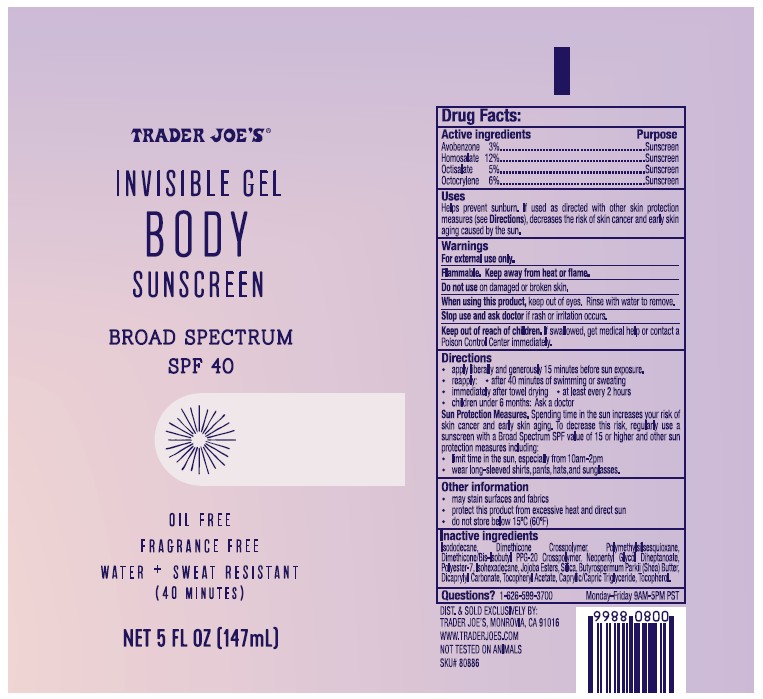 DRUG LABEL: TRADER JOES INVISIBLE BODY SUNSCREEN
NDC: 71270-159 | Form: GEL
Manufacturer: Trader Joe's Company
Category: otc | Type: HUMAN OTC DRUG LABEL
Date: 20250326

ACTIVE INGREDIENTS: OCTISALATE 5 g/100 mL; HOMOSALATE 12 g/100 mL; AVOBENZONE 3 g/100 mL; OCTOCRYLENE 6 g/100 mL
INACTIVE INGREDIENTS: ISODODECANE; TOCOPHEROL; SHEA BUTTER; SILICON DIOXIDE; DICAPRYLYL CARBONATE; DIMETHICONE CROSSPOLYMER (450000 MPA.S AT 12% IN CYCLOPENTASILOXANE); POLYMETHYLSILSESQUIOXANE (11 MICRONS); DIMETHICONE/BIS-ISOBUTYL PPG-20 CROSSPOLYMER; NEOPENTYL GLYCOL DIHEPTANOATE; POLYESTER-7; ISOHEXADECANE; HYDROGENATED JOJOBA OIL/JOJOBA OIL, RANDOMIZED (IODINE VALUE 40-44); .ALPHA.-TOCOPHEROL ACETATE; MEDIUM-CHAIN TRIGLYCERIDES

TRADER JOE’S (as PLD) - Invisible Gel Body Sunscreen SPF 40 (71270-159)

ACTIVE INGREDIENTS

AVOBENZONE 3%

HOMOSALATE 12%

OCTISALATE 5%

OCTOCRYLENE 6%

PURPOSE

SUNSCREEN

USES

HELPS PREVENT SUNSCREEN. IF USED AS DIRECTED WITH OTHER SUN PROTECTION MEASURES (SEE DIRECTIONS), DECREASES THE RISK OF SKIN CANCER AND EARLY SKIN AGING CAUSED BY THE SUN.

WARNINGS

For external use only.

Flammable. Keep away from heat or flame.

Do not use on damaged or broken skin.

When using this product, keep out of eyes. Rinse with water to remove.

Stop use and ask a doctor if rash occurs.

Keep out of reach of children. If swallowed, get medical help or contact a Poison Control Center immediately.

DIRECTIONS

- Apply liberally and generously 15 minutes before sun exposure.
- Reapply:
- after 40 minutes of swimming or sweating
- immediately after towel drying
- at least every 2 hours.
- Children under 6 months: ask a doctor.

Sun Protection Measures. Spending time in the sun increases your risk of skin cancer and early skin aging. To decrease this risk, regularly use a sunscreen with a Broad Spectrum SPF 15 value or higher along with other sun protection measures including:

- limit time in the sun, especially from 10 a.m. – 2 p.m.
- wear long-sleeved shirts, pants, hats and sunglasses.

OTHER INFORMATION

- May stain surfaces and fabrics
- Protect this product from excessive heat and direct sun
- Do not store below 15°C (60°F).

INACTIVE INGREDIENTS

ISODODECANE, DIMETHICONE CROSSPOLYMER, POYMETHYLSILSESQUIOXANE, DIMETHICONE/BIS-ISOBUTYL PPG-20 CROSSPOLYMER, NEOPENTYL GLYCOL DIHEPTANOATE, POLYESTER-7, ISOHEXADECANE, JOJOBA ESTERS, SILICA, BUTYROSPERMUM PARKII (SHEA) BUTTER, DICAPRYLYL CARBONATE, TOCOPHERYL ACETATE, CAPRYLIC/CAPRIC TRIGLYCERIDE, TOCOPHEROL

QUESTIONS?

1- 626-599-3700

Monday – Friday 9 AM – 5 PM PST